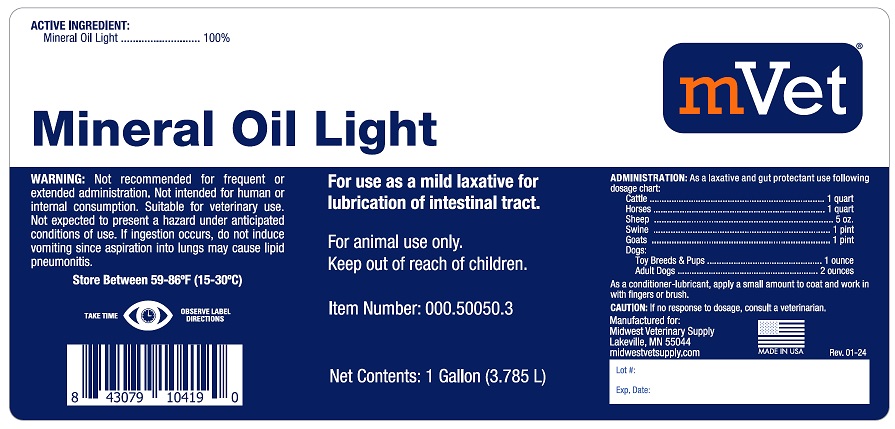 DRUG LABEL: Mineral Oil Light
NDC: 86223-044 | Form: LIQUID
Manufacturer: Midwest Veterinary Supply, Inc.
Category: animal | Type: OTC ANIMAL DRUG LABEL
Date: 20251126

ACTIVE INGREDIENTS: LIGHT MINERAL OIL 3.785 L/3.785 L

WARNINGS AND PRECAUTIONS

Mineral Oil Light

ACTIVE INGREDIENTS:

Mineral Oil Light................. 100%

For use as a mild laxative for lubrication of intestinal tract.

For animal use only.

Keep out of reach of children.

WARNING: Not recommended for frequent repeated or extended administration. Not intended for human or internal consumption. Suitable for veterinary use. Not expected to present a hazard under anticipated conditions of use. If ingestion occurs, do not induce vomiting since aspiration into lungs may cause lipid pneumonitis.

Store Between 59-89°F (15-30°C)

ADMINISTRATION: As a laxative and gut protectant use following dosage chart:

Cattle.................................1 quart

Horses................................1 quart

Sheep................................5 oz

Swine................................1 pint

Goats................................1 pint

Dogs:

Toy Breeds & Pups............1 ounce

Adult Dogs......................2 ounce

As a conditioner-lubricant, apply s small amount to coat and work in fingers or brush.

CAUTION: If no response to dosage, consult a veterinarian.

Manufactured for:

Midwest Veterinary Supply

Lakeville, MN 55044

Midwestvetsupply.com

MADE IN USA